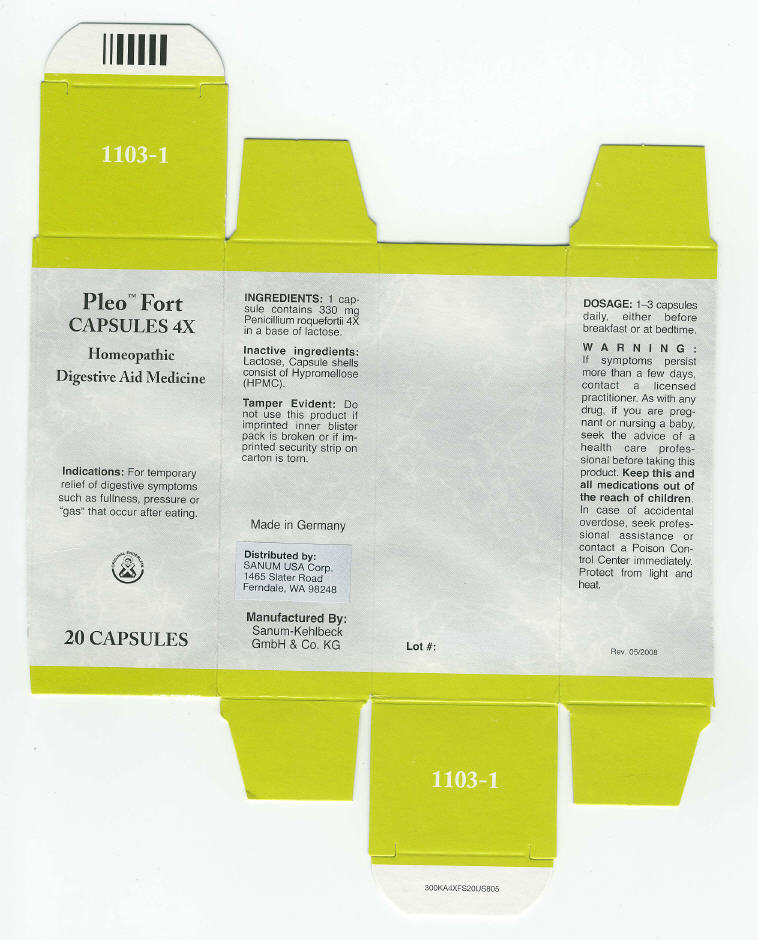 DRUG LABEL: Pleo Fort
NDC: 60681-1103 | Form: CAPSULE
Manufacturer: Sanum Kehlbeck GmbH & Co. KG
Category: homeopathic | Type: HUMAN OTC DRUG LABEL
Date: 20091009

ACTIVE INGREDIENTS: penicillium roqueforti 4 [HP_X]/1 1
INACTIVE INGREDIENTS: lactose; hypromellose

Pleo™ Fort
CAPSULES 4X

Homeopathic Digestive Aid Medicine

20 CAPSULES

Indications

For temporary relief of digestive symptoms such as fullness, pressure or "gas" that occur after eating.

INGREDIENTS

1 capsule contains 330 mg Penicillium roquefortii 4X in a base of lactose.

Inactive ingredients

Lactose, Capsule shells consist of Hypromellose (HPMC).

Tamper Evident

Do not use this product if imprinted inner blister pack is broken or if imprinted security strip on carton is torn.

DOSAGE

1–3 capsules daily, either before breakfast or at bedtime.

WARNING

If symptoms persist more than a few days, contact a licensed practitioner. As with any drug, if you are pregnant or nursing a baby, seek the advice of a health care professional before taking this product.

KEEP OUT OF REACH OF CHILDREN

Keep this and all medications out of the reach of children. In case of accidental overdose, seek professional assistance or contact a Poison Control Center immediately.

STORAGE AND HANDLING

Protect from light and heat.

Made in Germany

Distributed by:
SANUM USA Corp.
1465 Slater Road
Ferndale, WA 98248

Manufactured By:
Sanum-Kehlbeck
GmbH & Co. KG

Rev. 05/2008

PRINCIPAL DISPLAY PANEL - Capsule Carton

Pleo™ Fort
CAPSULES 4X

Homeopathic
Digestive Aid Medicine

Indications: For temporary
relief of digestive symptoms
such as fullness, pressure or
"gas" that occur after eating.

ORIGINAL ENDERLEIN

20 CAPSULES